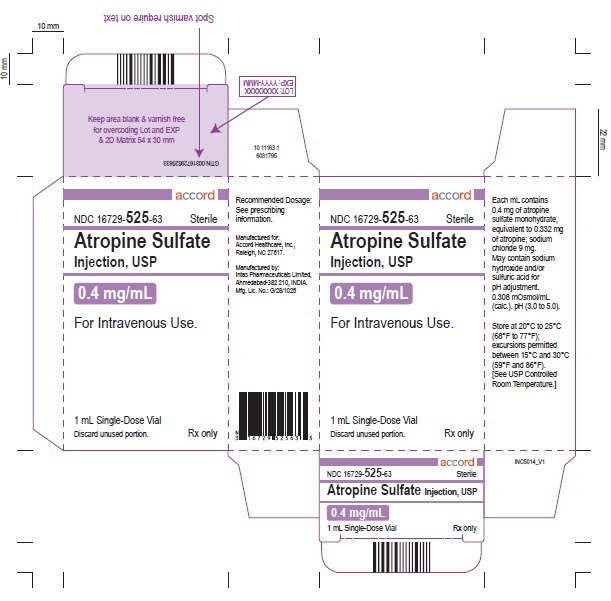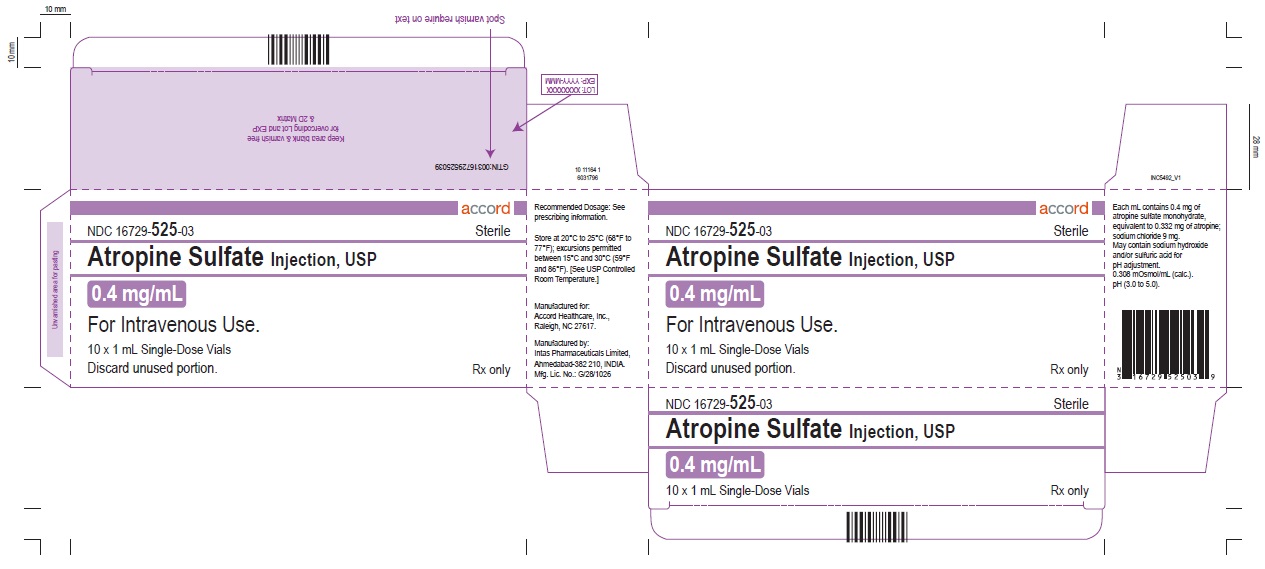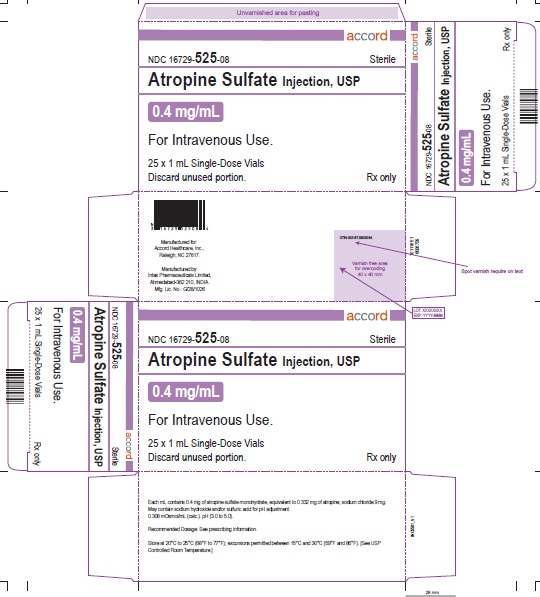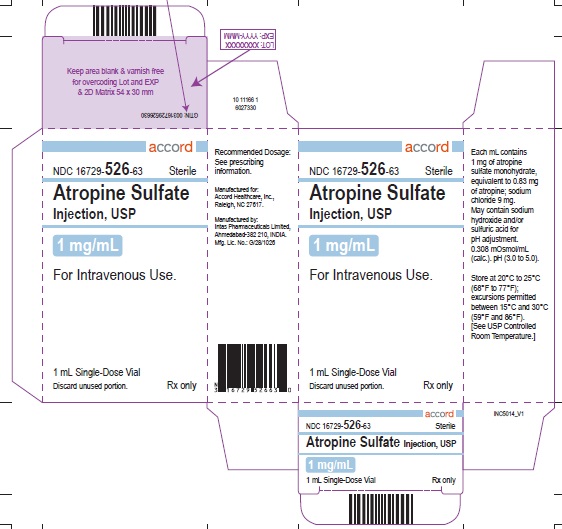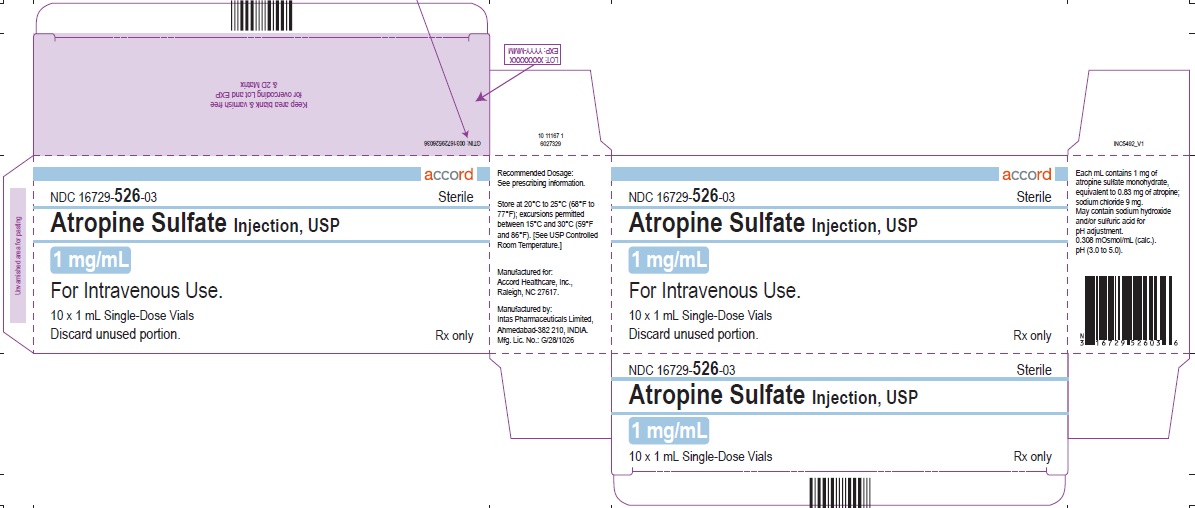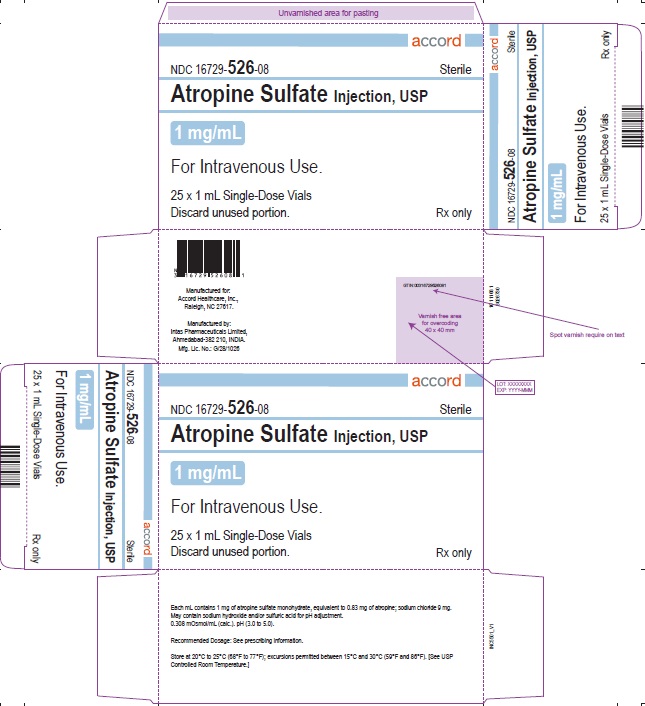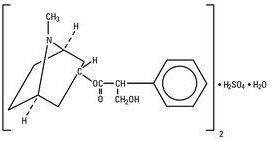 DRUG LABEL: ATROPINE SULFATE
NDC: 16729-525 | Form: INJECTION, SOLUTION
Manufacturer: Accord Healthcare Inc.
Category: prescription | Type: HUMAN PRESCRIPTION DRUG LABEL
Date: 20250228

ACTIVE INGREDIENTS: ATROPINE SULFATE 0.4 mg/1 mL
INACTIVE INGREDIENTS: SODIUM CHLORIDE 9 mg/1 mL; SODIUM HYDROXIDE; SULFURIC ACID; WATER

HIGHLIGHTS OF PRESCRIBING INFORMATION

These highlights do not include all the information needed to use ATROPINE SULFATE INJECTIONsafely and effectively. See full prescribing information for ATROPINE SULFATE INJECTION.
ATROPINE SULFATE INJECTION, for intravenous use
Initial U.S. Approval: 1960

1 INDICATIONS AND USAGE

Atropine is a muscarinic antagonist indicated for temporary blockade of severe or life threatening muscarinic effects. (1)

2 DOSAGE AND ADMINISTRATION

- For intravenous administration (2.1)
- Titrate according to heart rate, PR interval, blood pressure and symptoms (2.1)
- Adult dosage
  - Antisialagogue or for antivagal effects: Initial single dose of 0.5 to 1 mg (2.2)
  - Antidote for organophosphorus or muscarinic mushroom poisoning: Initial single dose of 2 to 3 mg, repeated every 20-30 minutes (2.2)
  - Bradyasystolic cardiac arrest: 1 mg dose, repeated every 3-5 minutes if asystole persists (2.2)
- Patients with Coronary Artery Disease: Limit the total dose to 0.03 to 0.04 mg/kg (2.4)

3 DOSAGE FORMS AND STRENGTHS

Injection: 0.4 or 1 mg/mL as a clear, colorless solution in a single-dose vial.

4 CONTRAINDICATIONS

None. (4)

5 WARNINGS AND PRECAUTIONS

- Tachycardia (5.1)
- Glaucoma (5.2)
- Pyloric obstruction (5.3)
- Worsening urinary retention (5.4)
- Viscid bronchial plugs (5.5)

6 ADVERSE REACTIONS

Most adverse reactions are directly related to atropine's antimuscarinic action. Dryness of the mouth, blurred vision, photophobia and tachycardia commonly occur with chronic administration of therapeutic doses. (6)

To report SUSPECTED ADVERSE REACTIONS, contact Accord Healthcare Inc. at 1-866-941-7875 or FDA at 1-800-FDA-1088 or www.fda.gov/medwatch.

7 DRUG INTERACTIONS

Mexiletine:Decreases rate of mexiletine absorption. (7.1)

FULL PRESCRIBING INFORMATION

1 INDICATIONS AND USAGE

Atropine Sulfate Injection, USP, is indicated for temporary blockade of severe or life threatening muscarinic effects, e.g., as an antisialagogue, an antivagal agent, an antidote for organophosphorus or muscarinic mushroom poisoning, and to treat bradyasystolic cardiac arrest.

2 DOSAGE AND ADMINISTRATION

2.1 General Administration

Parenteral drug products should be inspected visually for particulate matter and discoloration prior to administration, whenever solution and container permit. Do not administer unless solution is clear and seal is intact. Each vial is intended for single dose only. Discard unused portion.

For intravenous administration.

Titrate based on heart rate, PR interval, blood pressure and symptoms.

2.2 Adult Dosage

Table 1: Recommended Dosage
Use | Dose (adults) | Repeat
Antisialagogue or other antivagal | 0.5 to 1 mg | 1-2 hours
Organophosphorus or muscarinic mushroom poisoning | 2 to 3 mg | 20-30 minutes
Bradyasystolic cardiac arrest | 1 mg | 3-5 minutes; 3 mg maximum total dose

2.3 Pediatric Dosage

Dosing in pediatric populations has not been well studied. Usual initial dose is 0.01 to 0.03 mg/kg.

2.4 Dosing in Patients with Coronary Artery Disease

Limit the total dose of atropine sulfate to 0.03 to 0.04 mg/kg [see Warnings and Precautions (5.1)].

3 DOSAGE FORMS AND STRENGTHS

Injection: supplied as a clear, colorless solution in a 1 mL glass vial in the following concentrations;

- 0.4 mg/mL: containing 0.4 mg of atropine sulfate monohydrate equivalent to 0.332 mg of atropine.
- 1 mg/mL: containing 1 mg of atropine sulfate monohydrate equivalent to 0.83 mg of atropine.

4 CONTRAINDICATIONS

None.

5 WARNINGS AND PRECAUTIONS

5.1 Tachycardia

When the recurrent use of atropine is essential in patients with coronary artery disease, the total dose should be restricted to 2 to 3 mg (maximum 0.03 to 0.04 mg/kg) to avoid the detrimental effects of atropine-induced tachycardia on myocardial oxygen demand.

5.2 Acute Glaucoma

Atropine may precipitate acute glaucoma.

5.3 Pyloric Obstruction

Atropine may convert partial organic pyloric stenosis into complete obstruction.

5.4 Complete Urinary Retention

Atropine may lead to complete urinary retention in patients with prostatic hypertrophy.

5.5 Viscid Plugs

Atropine may cause inspissation of bronchial secretions and formation of viscid plugs in patients with chronic lung disease.

6 ADVERSE REACTIONS

The following adverse reactions have been identified during post-approval use of atropine sulfate. Because these reactions are reported voluntarily from a population of uncertain size, it is not always possible to reliably estimate their frequency or establish a causal relationship to drug exposure.

Most of the side effects of atropine are directly related to its antimuscarinic action. Dryness of the mouth, blurred vision, photophobia and tachycardia commonly occur. Anhidrosis can produce heat intolerance. Constipation and difficulty in micturition may occur in elderly patients. Occasional hypersensitivity reactions have been observed, especially skin rashes which in some instances progressed to exfoliation.

7 DRUG INTERACTIONS

7.1 Mexiletine

Atropine Sulfate Injection decreased the rate of mexiletine absorption without altering the relative oral bioavailability; this delay in mexiletine absorption was reversed by the combination of atropine and intravenous metoclopramide during pretreatment for anesthesia.

8 USE IN SPECIFIC POPULATIONS

8.1 Pregnancy

Risk Summary

There are risks to the mother and fetus associated with untreated severe or life-threatening muscarinic events (see Clinical Considerations). Available data from published observational studies on atropine use in pregnant women are insufficient to evaluate for a drug-associated risk of major birth defects, miscarriage, or adverse maternal or fetal outcomes (see Data). Animal reproduction studies have not been conducted with atropine.

Clinical Considerations

Disease-associated maternal and/or embryo/fetal risk

Severe or life-threatening muscarinic events such as acute organophosphate poisoning and symptomatic bradycardia are medical emergencies in pregnancy which can be fatal if left untreated. Life-sustaining therapy for the pregnant woman should not be withheld because of concerns regarding the effects of atropine on the fetus.

Data

Human Data

Atropine crosses the placenta [see Clinical Pharmacology (12.3)] . No adequate and well-controlled studies are available regarding use of atropine in pregnant women. In a cohort study of 401 pregnancies in the first trimester and 797 pregnancies in the second or third trimester, atropine use was not associated with an increased risk of congenital malformation. In a surveillance study, 381 newborns were exposed to atropine during the first trimester; 18 major birth defects were observed when 16 were expected. No specific pattern of major birth defects was identified. In another surveillance study of 50 pregnancies in the first trimester, atropine use was not associated with an increased risk of malformations.

Methodological limitations of these observational studies including the inability to control for the dosage and timing of atropine exposure, underlying maternal disease, or concomitant maternal drug use, cannot definitively establish or exclude any drug associated risk during pregnancy.

8.2 Lactation

Risk Summary

Trace amounts of atropine have been reported in human milk after oral intake. There are no available data on atropine levels in human milk after intravenous injection, the effects on the breastfed infant, or the effects on milk production.

Clinical Considerations

Minimizing exposure

The elimination half-life of atropine is more than doubled in children less than 2 years of age [see Clinical Pharmacology (12.3)]. To minimize potential infant exposure to Atropine Sulfate Injection, a woman may pump and discard her milk for 24 hours after use before resuming to breastfeed her infant.

8.4 Pediatric Use

Recommendations for use in pediatric patients are not based on clinical trials.

8.5 Geriatric Use

An evaluation of current literature revealed no clinical experience identifying differences in response between elderly and younger patients. In general, dose selection for an elderly patient should be cautious, usually starting at the low end of the dosing range, reflecting the greater frequency of decreased hepatic, renal, or cardiac function, and of concomitant disease or other drug therapy.

10 OVERDOSAGE

Excessive dosing may cause palpitation, dilated pupils, difficulty in swallowing, hot dry skin, thirst, dizziness, restlessness, tremor, fatigue and ataxia. Toxic doses lead to restlessness and excitement, hallucinations, delirium and coma. Depression and circulatory collapse occur only with severe intoxication. In such cases, blood pressure declines and death due to respiratory failure may ensue following paralysis and coma.

The fatal adult dose of atropine is not known. In pediatric populations, 10 mg or less may be fatal.

In the event of toxic overdosage, a short acting barbiturate or diazepam may be given as needed to control marked excitement and convulsions. Large doses for sedation should be avoided because central depressant action may coincide with the depression occurring late in atropine poisoning. Central stimulants are not recommended.

Physostigmine, given as an atropine antidote by slow intravenous injection of 1 to 4 mg (0.5 to 1 mg in pediatric populations), rapidly abolishes delirium and coma caused by large doses of atropine. Since physostigmine is rapidly destroyed, the patient may again lapse into coma after one to two hours, and repeated doses may be required.

Artificial respiration with oxygen may be necessary. Ice bags and alcohol sponges help to reduce fever, especially in pediatric populations.

Atropine is not removed by dialysis.

11 DESCRIPTION

Atropine Sulfate Injection, USP is a sterile, nonpyrogenic isotonic solution of atropine sulfate monohydrate in water for injection with sodium chloride sufficient to render the solution isotonic. It is administered parenterally by intravenous injection.

Each milliliter (mL) contains 0.4 mg or 1 mg of atropine sulfate monohydrate equivalent to 0.332 mg or 0.83 mg of atropine, and sodium chloride, 9 mg. May contain sodium hydroxide and/or sulfuric acid for pH adjustment.
0.308 mOsmol/mL (calc.). pH 3.0 to 5.0.

The solution contains no bacteriostat, antimicrobial agent or added buffer (except for pH adjustment) and is intended for use only as a single-dose injection. When smaller doses are required the unused portion should be discarded.

Atropine Sulfate, USP is chemically designated 1α H, 5α H-Tropan-3-α-ol (±)-tropate (ester), sulfate (2:1) (salt) monohydrate, (C17H23NO3)2H2SO4H2O, colorless crystals or white crystalline powder very soluble in water. It has the following structural formula:

Atropine, a naturally occurring belladonna alkaloid, is a racemic mixture of equal parts of d- and 1-hyocyamine, whose activity is due almost entirely to the levo isomer of the drug.

12 CLINICAL PHARMACOLOGY

12.1 Mechanism of Action

Atropine is an antimuscarinic agent since it antagonizes the muscarine-like actions of acetylcholine and other choline esters.

Atropine inhibits the muscarinic actions of acetylcholine on structures innervated by postganglionic cholinergic nerves, and on smooth muscles which respond to endogenous acetylcholine but are not so innervated. As with other antimuscarinic agents, the major action of atropine is a competitive or surmountable antagonism which can be overcome by increasing the concentration of acetylcholine at receptor sites of the effector organ (e.g., by using anticholinesterase agents which inhibit the enzymatic destruction of acetylcholine). The receptors antagonized by atropine are the peripheral structures that are stimulated or inhibited by muscarine (i.e., exocrine glands and smooth and cardiac muscle). Responses to postganglionic cholinergic nerve stimulation also may be inhibited by atropine but this occurs less readily than with responses to injected (exogenous) choline esters.

12.2 Pharmacodynamics

Atropine-induced parasympathetic inhibition may be preceded by a transient phase of stimulation, especially on the heart where small doses first slow the rate before characteristic tachycardia develops due to paralysis of vagal control. Atropine exerts a more potent and prolonged effect on heart, intestine and bronchial muscle than scopolamine, but its action on the iris, ciliary body and certain secretory glands is weaker than that of scopolamine. Unlike the latter, atropine in clinical doses does not depress the central nervous system but may stimulate the medulla and higher cerebral centers. Although mild vagal excitation occurs, the increased respiratory rate and (sometimes) increased depth of respiration produced by atropine are more probably the result of bronchiolar dilatation. Accordingly, atropine is an unreliable respiratory stimulant and large or repeated doses may depress respiration.

Adequate doses of atropine abolish various types of reflex vagal cardiac slowing or asystole. The drug also prevents or abolishes bradycardia or asystole produced by injection of choline esters, anticholinesterase agents or other parasympathomimetic drugs, and cardiac arrest produced by stimulation of the vagus. Atropine also may lessen the degree of partial heart block when vagal activity is an etiologic factor. In some patients with complete heart block, the idioventricular rate may be accelerated by atropine; in others, the rate is stabilized. Occasionally a large dose may cause atrioventricular (A-V) block and nodal rhythm.

Atropine Sulfate Injection, USP in clinical doses counteracts the peripheral dilatation and abrupt decrease in blood pressure produced by choline esters. However, when given by itself, atropine does not exert a striking or uniform effect on blood vessels or blood pressure. Systemic doses slightly raise systolic and lower diastolic pressures and can produce significant postural hypotension. Such doses also slightly increase cardiac output and decrease central venous pressure. Occasionally, therapeutic doses dilate cutaneous blood vessels, particularly in the "blush" area (atropine flush), and may cause atropine "fever" due to suppression of sweat gland activity in infants and small children.

The effects of intravenous atropine on heart rate (maximum heart rate) and saliva flow (minimum flow) after intravenous administration (rapid, constant infusion over 3 min.) are delayed by 7 to 8 minutes after drug administration and both effects are non-linearly related to the amount of drug in the peripheral compartment. Changes in plasma atropine levels following intramuscular administration (0.5 to 4 mg doses) and heart rate are closely overlapped but the time course of the changes in atropine levels and behavioral impairment indicates that pharmacokinetics is not the primary rate-limiting mechanism for the central nervous system effect of atropine.

12.3 Pharmacokinetics

Atropine disappears rapidly from the blood following injection and is distributed throughout the body. Exercise, both prior to and immediately following intramuscular administration of atropine, significantly increases the absorption of atropine due to increased perfusion in the muscle and significantly decreases the clearance of atropine. The pharmacokinetics of atropine is nonlinear after intravenous administration of 0.5 to 4 mg. Atropine's plasma protein binding is about 44% and saturable in the 2-20 μg/mL concentration range. Atropine readily crosses the placental barrier and enters the fetal circulation, but is not found in amniotic fluid. Much of the drug is destroyed by enzymatic hydrolysis, particularly in the liver; from 13 to 50% is excreted unchanged in the urine. Traces are found in various secretions, including milk. The major metabolites of atropine are noratropine, atropin-n-oxide, tropine, and tropic acid. The metabolism of atropine is inhibited by organophosphate pesticides.

Specific Populations

The elimination half-life of atropine is more than doubled in children under two years and the elderly (>65 years old) compared to other age groups. There is no gender effect on the pharmacokinetics and pharmacodynamics (heart rate changes) of atropine.

13 NONCLINICAL TOXICOLOGY

13.1 Carcinogenesis, Mutagenesis, Impairment of Fertility

Studies have not been performed to evaluate the carcinogenic or mutagenic potential of atropine or its potential to affect fertility adversely.

16 HOW SUPPLIED/STORAGE AND HANDLING

Atropine Sulfate Injection, USP 0.4 and 1 mg/mL are supplied in 1 mL, single-dose glass vials as follows:

Table 2: How Supplied

Concentration (mg/mL) | Package Size | NDC #
0.4 mg/mL | 1 Vial | 16729-525-63
0.4 mg/mL | 10 Vials | 16729-525-03
0.4 mg/mL | 25 Vials | 16729-525-08
1 mg/mL | 1 Vial | 16729-526-63
1 mg/mL | 10 Vials | 16729-526-03
1 mg/mL | 25 Vials | 16729-526-08

Store at 20°C to 25°C (68°F to 77°F); excursions permitted between 15°C and 30°C (59°F and 86°F). [See USP Controlled Room Temperature.]

Manufactured For:
Accord Healthcare, Inc.,
8041 Arco Corporate Drive,
Suite 200,
Raleigh, NC 27617,
USA.

Manufactured By:
Intas Pharmaceuticals Limited,
Ahmedabad-380 054, India.

10 4020 2 6026794

November 2023